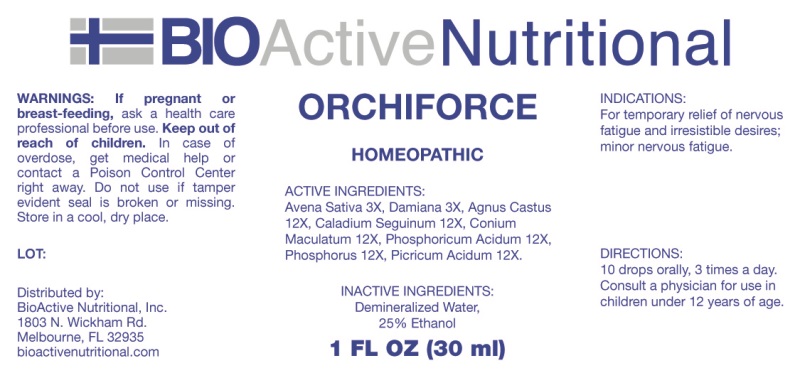 DRUG LABEL: Orchiforce
NDC: 43857-0363 | Form: LIQUID
Manufacturer: BioActive Nutritional, Inc.
Category: homeopathic | Type: HUMAN OTC DRUG LABEL
Date: 20241017

ACTIVE INGREDIENTS: AVENA SATIVA FLOWERING TOP 3 [hp_X]/1 mL; TURNERA DIFFUSA LEAFY TWIG 3 [hp_X]/1 mL; CHASTE TREE 12 [hp_X]/1 mL; DIEFFENBACHIA SEGUINE 12 [hp_X]/1 mL; CONIUM MACULATUM FLOWERING TOP 12 [hp_X]/1 mL; PHOSPHORIC ACID 12 [hp_X]/1 mL; PHOSPHORUS 12 [hp_X]/1 mL; PICRIC ACID 12 [hp_X]/1 mL
INACTIVE INGREDIENTS: WATER; ALCOHOL

DRUG FACTS:

ACTIVE INGREDIENTS:

Avena Sativa 3X, Damiana 3X, Agnus Castus 12X, Caladium Seguinum 12X, Conium Maculatum 12X, Phosphoricum Acidum 12X, Phosphorus 12X, Picricum Acidum 12X.

INDICATIONS:

For temporary relief of nervous fatigue and irresistible desires; minor nervous fatigue.

WARNINGS:

If pregnant or breast-feeding, ask a health care professional before use.

Keep out of reach of children. In case of overdose, get medical help or contact a Poison Control Center right away.

Do not use if tamper evident seal is broken or missing.

Store in a cool, dry place.

Keep out of reach of children. In case of overdose, get medical help or contact a Poison Control Center right away.

DIRECTIONS:

10 drops orally, 3 times a day. Consult a physician for use in children under 12 years of age.

INDICATIONS:

For temporary relief of nervous fatigue and irresistible desires; minor nervous fatigue.

INACTIVE INGREDIENTS:

Demineralized Water, 25% Ethanol.

QUESTIONS:

Distributed by:

BioActive Nutritional, Inc.

1803 N. Wickham Rd.

Melbourne, FL 32935

bioactivenutritional.com

PACKAGE LABEL DISPLAY:

BioActive Nutritional

ORCHIFORCE

Homeopathic

1 FL OZ (30 ml)